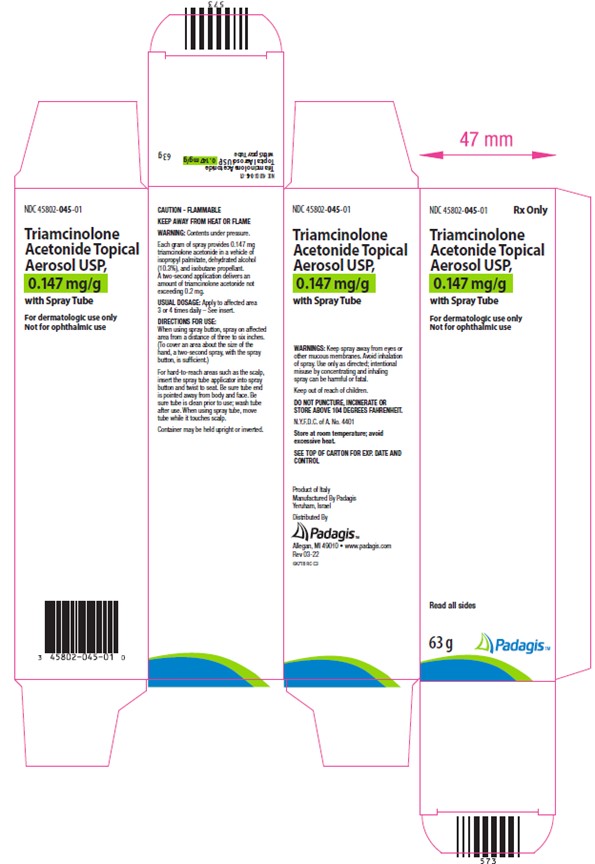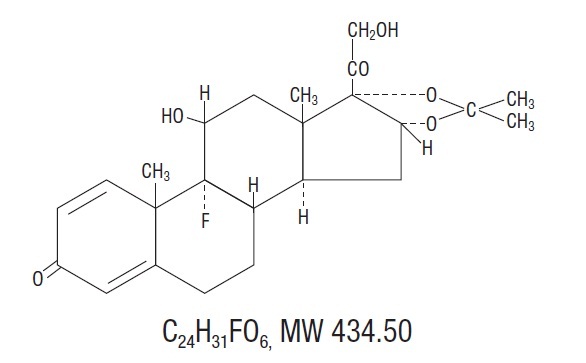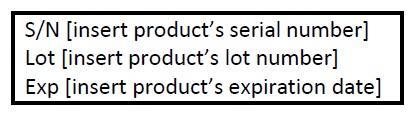 DRUG LABEL: Triamcinolone Acetonide
NDC: 45802-045 | Form: AEROSOL, SPRAY
Manufacturer: Padagis Israel Pharmaceuticals Ltd
Category: prescription | Type: HUMAN PRESCRIPTION DRUG LABEL
Date: 20230501

ACTIVE INGREDIENTS: TRIAMCINOLONE ACETONIDE 0.147 mg/1 g
INACTIVE INGREDIENTS: ISOPROPYL PALMITATE; ALCOHOL

Triamcinolone Acetonide Topical Aerosol USP, 0.147 mg/g

Rx only

For dermatologic use only

Not for ophthalmic use

DESCRIPTION

The topical corticosteroids constitute a class of primarily synthetic steroids used as anti-inflammatory and antipruritic agents. The steroids in this class include triamcinolone acetonide. Triamcinolone acetonide is designated chemically as 9-fluoro-11β, 16α, 17, 21-tetrahydroxypregna-1, 4-diene-3, 20-dione cyclic 16, 17-acetal with acetone. The structural formula is:

A two-second application, which covers an area approximately the size of the hand, delivers an amount of triamcinolone acetonide not exceeding 0.2 mg. After spraying, the nonvolatile vehicle remaining on the skin contains approximately 0.2% triamcinolone acetonide. Each gram of spray provides 0.147 mg triamcinolone acetonide in a vehicle of isopropyl palmitate, dehydrated alcohol (10.3%), and isobutane propellant.

CLINICAL PHARMACOLOGY

Topical corticosteroids share anti-inflammatory, antipruritic and vasoconstrictive actions.

The mechanism of anti-inflammatory activity of the topical corticosteroids is unclear. Various laboratory methods, including vasoconstrictor assays, are used to compare and predict potencies and/or clinical efficacies of the topical corticosteroids. There is some evidence to suggest that a recognizable correlation exists between vasoconstrictor potency and therapeutic efficacy in man.

Pharmacokinetics

The extent of percutaneous absorption of topical corticosteroids is determined by many factors including the vehicle, the integrity of the epidermal barrier, and the use of occlusive dressings.

Topical corticosteroids can be absorbed from normal intact skin. Inflammation and/or other disease processes in the skin increase percutaneous absorption.

Once absorbed through the skin, topical corticosteroids are handled through pharmacokinetic pathways similar to systemically administered corticosteroids. Corticosteroids are bound to plasma proteins in varying degrees. Corticosteroids are metabolized primarily in the liver and are then excreted by the kidneys. Some of the topical corticosteroids and their metabolites are also excreted into the bile.

INDICATIONS AND USAGE

Triamcinolone Acetonide Topical Aerosol USP, 0.147 mg/g is indicated for relief of the inflammatory and pruritic manifestations of corticosteroid-responsive dermatoses.

CONTRAINDICATIONS

Topical corticosteroids are contraindicated in those patients with a history of hypersensitivity to any of the components of the preparations.

PRECAUTIONS

General

Systemic absorption of topical corticosteroids has produced reversible hypothalamic-pituitary-adrenal (HPA) axis suppression, manifestations of Cushing’s syndrome, hyperglycemia, and glucosuria in some patients.

Conditions which augment systemic absorption include the application of the more potent steroids, use over large surface areas, prolonged use, and the addition of occlusive dressings.

Therefore, patients receiving a large dose of any potent topical steroid applied to a large surface area or under an occlusive dressing should be evaluated periodically for evidence of HPA axis suppression by using the urinary free cortisol and ACTH stimulation tests, and for impairment of thermal homeostasis. If HPA axis suppression or elevation of the body temperature occurs, an attempt should be made to withdraw the drug, to reduce the frequency of application, substitute a less potent steroid, or use a sequential approach.

Recovery of HPA axis function and thermal homeostasis are generally prompt and complete upon discontinuation of the drug. Infrequently, signs and symptoms of steroid withdrawal may occur, requiring supplemental systemic corticosteroids.

Children may absorb proportionally larger amounts of topical corticosteroids and thus be more susceptible to systemic toxicity (see PRECAUTIONS, Pediatric Use).

If irritation develops, topical corticosteroids should be discontinued and appropriate therapy instituted.

In the presence of dermatological infections, the use of an appropriate antifungal or antibacterial agent should be instituted. If a favorable response does not occur promptly, the corticosteroid should be discontinued until the infection has been adequately controlled.

Information for the Patient

Patients using Triamcinolone Acetonide Topical Aerosol USP, 0.147 mg/g should receive the following information and instructions:

1. This medication is to be used as directed by the physician. It is for external use only; avoid contact with the eyes and inhalation of the spray.

2. Patients should be advised not to use this medication for any disorder other than for which it was prescribed.

3. The treated skin area should not be bandaged or otherwise covered or wrapped as to be occlusive unless directed by the physician.

4. Patients should report any signs of local adverse reactions.

5. Parents of pediatric patients should be advised not to use tight-fitting diapers or plastic pants on a child being treated in the diaper area, as these garments may constitute occlusive dressings.

6. Do not use Triamcinolone Acetonide Topical Aerosol USP, 0.147 mg/g on the underarms or groin areas unless directed by your physician.

7. If no improvement is seen within 2 weeks, contact your physician.

8. Do not use other corticosteroid-containing products while using Triamcinolone Acetonide Topical Aerosol USP, 0.147 mg/g without first consulting your physician.

9. Triamcinolone Acetonide Topical Aerosol USP, 0.147 mg/g is flammable. Avoid heat, flames or smoking when applying Triamcinolone Acetonide Topical Aerosol USP, 0.147 mg/g.

Laboratory Tests

A urinary free cortisol test and ACTH stimulation test may be helpful in evaluating HPA axis suppression.

Carcinogenesis, Mutagenesis, Impairment of Fertility

Long-term animal studies have not been performed to evaluate the carcinogenic potential or the effect on fertility of topical corticosteroids.

Studies to determine mutagenicity with prednisolone and hydrocortisone showed negative results.

Pregnancy: Teratogenic Effects

Category C. Corticosteroids are generally teratogenic in laboratory animals when administered systemically at relatively low dosage levels. The more potent corticosteroids have been shown to be teratogenic after dermal application in laboratory animals. There are no adequate and well-controlled studies in pregnant women on teratogenic effects from topically applied corticosteroids. Therefore, topical corticosteroids should be used during pregnancy only if the potential benefit justifies the potential risk to the fetus. Drugs of this class should not be used extensively on pregnant patients, in large amounts, or for prolonged periods of time.

Nursing Mothers

It is not known whether topical administration of corticosteroids could result in sufficient systemic absorption to produce detectable quantities in breast milk. Systemically administered corticosteroids are secreted into breast milk in quantities not likely to have a deleterious effect on the infant. Nevertheless, caution should be exercised when topical corticosteroids are administered to a nursing woman.

Pediatric Use

Pediatric patients may demonstrate greater susceptibility to topical corticosteroid-induced HPA axis suppression and Cushing’s syndrome than mature patients because of a larger skin surface area to body weight ratio.

HPA axis suppression, Cushing’s syndrome, and intracranial hypertension have been reported in children receiving topical corticosteroids. Manifestations of adrenal suppression in children include linear growth retardation, delayed weight gain, low plasma cortisol levels, and absence of response to ACTH stimulation. Manifestations of intracranial hypertension include bulging fontanelles, headaches, and bilateral papilledema.

Administration of topical corticosteroids to children should be limited to the least amount compatible with an effective therapeutic regimen. Chronic corticosteroid therapy may interfere with the growth and development of children.

ADVERSE REACTIONS

The following local adverse reactions are reported infrequently with topical corticosteroids, but may occur more frequently with the use of occlusive dressings (reactions are listed in an approximate decreasing order of occurrence): burning, itching, irritation, dryness, folliculitis, hypertrichosis, acneiform eruptions, hypopigmentation, perioral dermatitis, allergic contact dermatitis, maceration of the skin, secondary infection, skin atrophy, striae, and miliaria.

OVERDOSAGE

Topically applied corticosteroids can be absorbed in sufficient amounts to produce systemic effects (see PRECAUTIONS, General).

DOSAGE AND ADMINISTRATION

Directions for use of the spray can are provided on the label. The preparation may be applied to any area of the body, but when it is sprayed about the face, care should be taken to see that the eyes are covered, and that inhalation of the spray is avoided.

Spray is flammable; avoid heat, flame or smoking when using this product.

Three or four applications daily of Triamcinolone Acetonide Topical Aerosol USP, 0.147 mg/g are generally adequate.

HOW SUPPLIED

Triamcinolone Acetonide Topical Aerosol USP, 0.147 mg/g

63 g (NDC 45802-045-01) aerosol can.

100 g (NDC 45802-045-02) aerosol can.

Storage and Handling

Store at room temperature; avoid excessive heat. Contents under pressure; do not puncture or incinerate. Keep out of reach of children.

To report SUSPECTED ADVERSE REACTIONS, contact the FDA at 1-800-FDA-1088 or www.fda.gov/medwatch.

Manufactured By Padagis, Yeruham, Israel

Distributed By PadagisTM, Allegan, MI 49010 • www.padagis.com

Rev 03-22

6K700 RC J3

PACKAGE/LABEL PRINCIPAL DISPLAY PANEL – 100 g Carton

Rx Only

Triamcinolone Acetonide Topical Aerosol USP, 0.147 mg/g

with Spray Tube

For dermatologic use only

Not for ophthalmic use

Read all sides

100 g

The following image is a placeholder representing the product identifier that is either affixed or imprinted on the drug package label during the packaging operation.